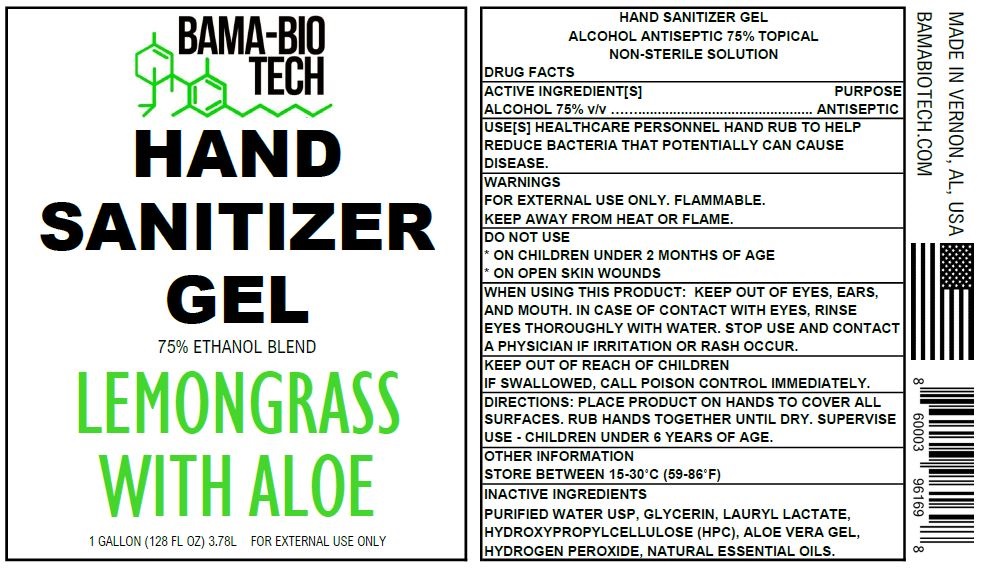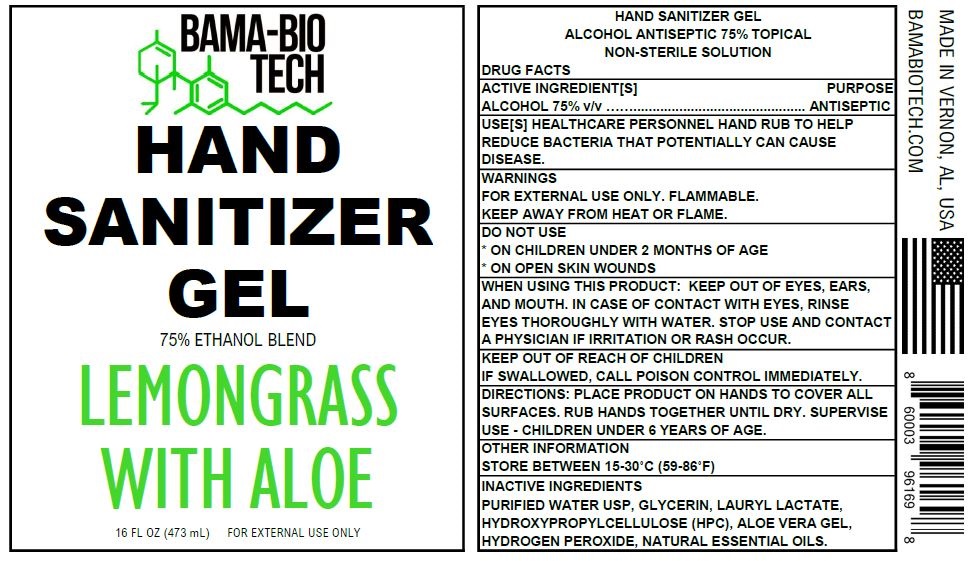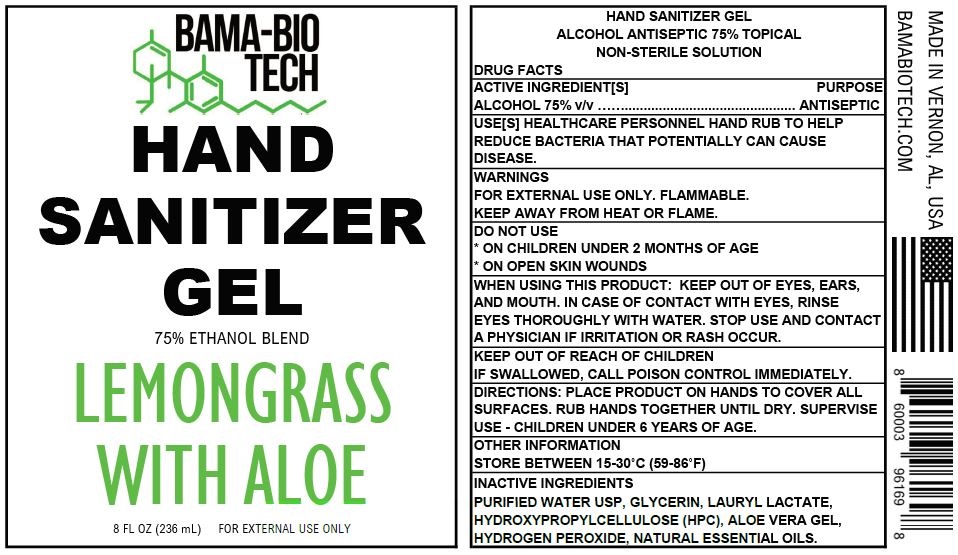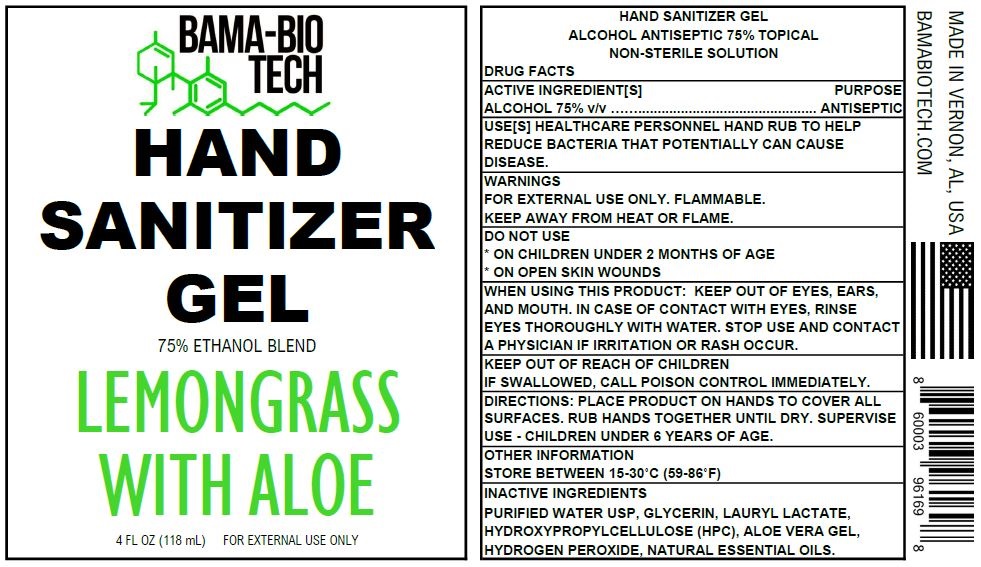 DRUG LABEL: Bama-Bio Tech Hand Sanitizer 75 Ethanol LemonGrass Scent
NDC: 90085-001 | Form: GEL
Manufacturer: Bama-Bio Tech Corporation
Category: otc | Type: HUMAN OTC DRUG LABEL
Date: 20220105

ACTIVE INGREDIENTS: ALCOHOL 0.75 mL/1 mL
INACTIVE INGREDIENTS: WATER; GLYCERIN; LAURYL LACTATE; HYDROXYPROPYL CELLULOSE, UNSPECIFIED; ALOE VERA LEAF; HYDROGEN PEROXIDE

Bama-Bio Tech Hand Sanitizer 75% Ethanol LemonGrass Scent

ACTIVE INGREDIENT[S]

ALCOHOL 75% v/v

PURPOSE

ANTISEPTIC

USE[S]

HEALTHCARE PERSONNEL HAND RUB TO HELP REDUCE BACTERIA THAT POTENTIALLY CAN CAUSE DISEASE.

WARNINGS

FOR EXTERNAL USE ONLY. FLAMMABLE. KEEP AWAY FROM HEAT OR FLAME.

DO NOT USE

- ON CHILDREN UNDER 2 MONTHS OF AGE
- ON OPEN SKIN WOUNDS

WHEN USING THIS PRODUCT

KEEP OUT OF EYES, EARS, AND MOUTH. IN CASE OF CONTACT WITH EYES, RINSE EYES THOROUGHLY WITH WATER.

STOP USE AND CONTACT A PHYSICIAN

IF IRRITATION OR RASH OCCUR.

KEEP OUT OF REACH OF CHILDREN

IF SWALLOWED, CALL POISON CONTROL IMMEDIATELY.

DIRECTIONS

PLACE PRODUCT ON HANDS TO COVER ALL SURFACES. RUB HANDS TOGETHER UNTIL DRY. SUPERVISE USE CHILDREN UNDER 6 YEARS OF AGE.

OTHER INFORMATION

STORE BETWEEN 15-30°C (59-86°F)

INACTIVE INGREDIENTS

PURIFIED WATER USP, GLYCERIN, LAURYL LACTATE, HYDROXYPROPYLCELLULOSE (HPC), ALOE VERA GEL, HYDROGEN PEROXIDE, NATURAL ESSENTIAL OILS.